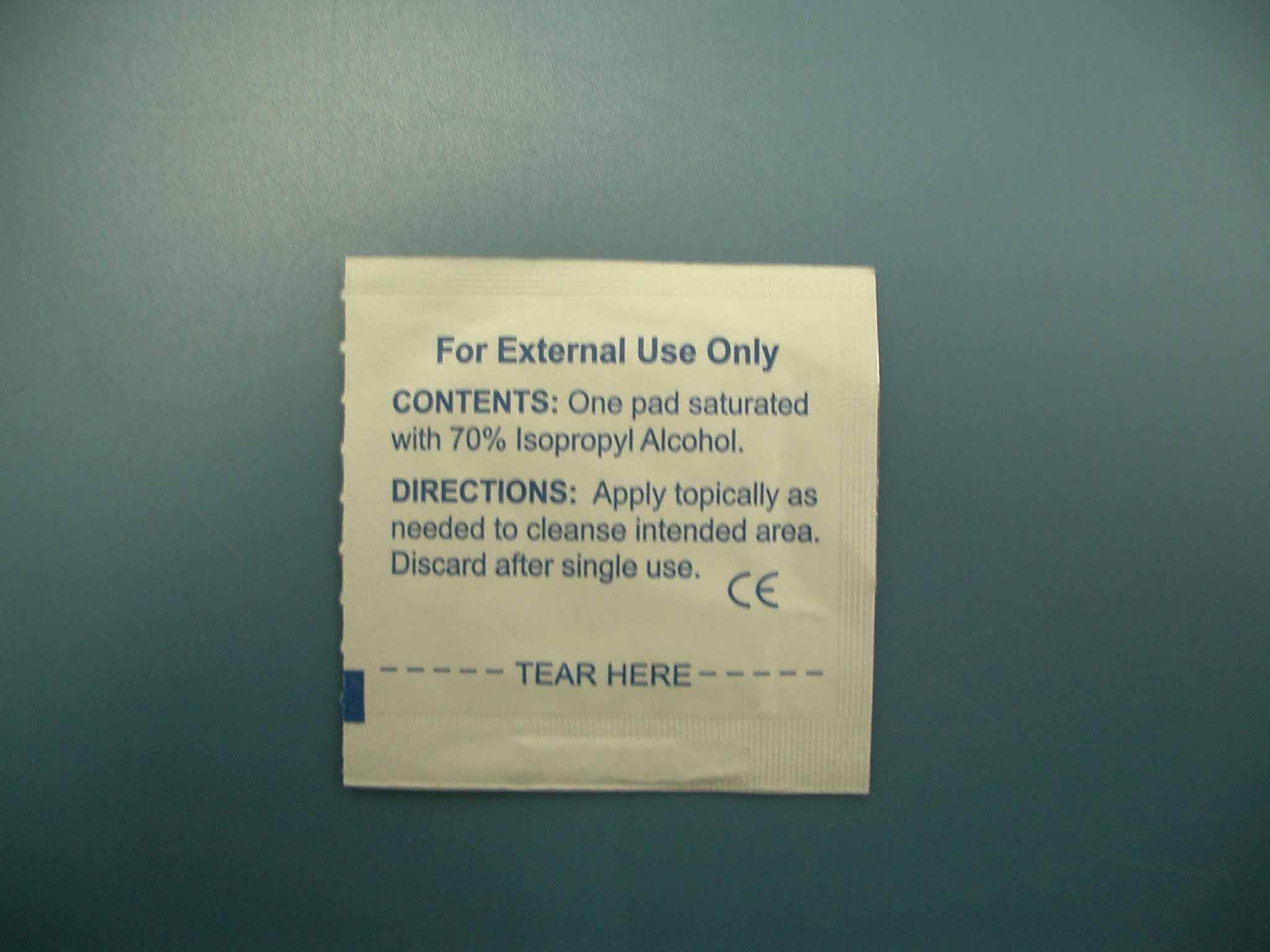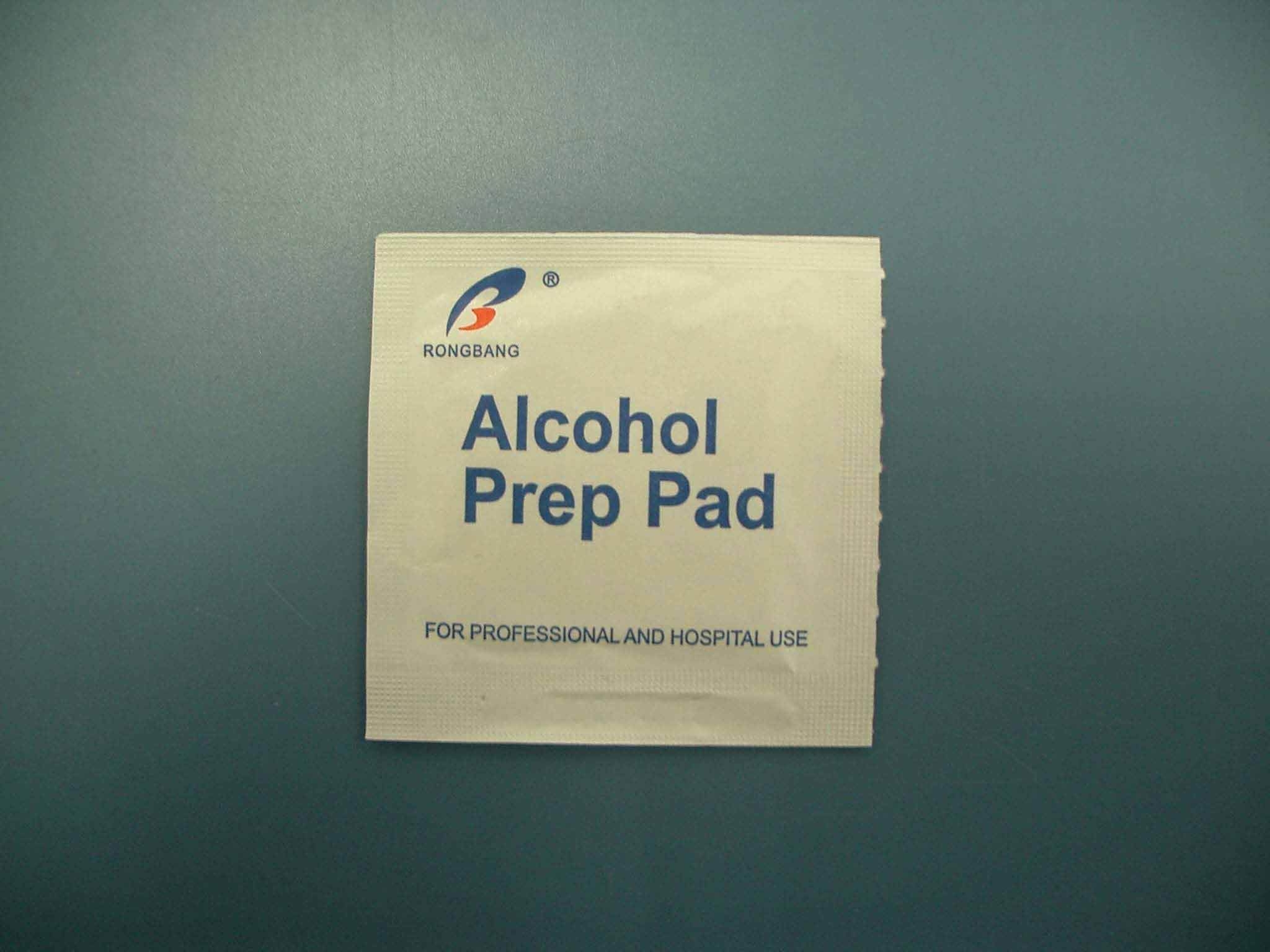 DRUG LABEL: Alcohol
NDC: 49953-2801 | Form: SWAB
Manufacturer: Dalian Rongbang Medical Healthy Devices Co., Ltd.
Category: otc | Type: HUMAN OTC DRUG LABEL
Date: 20231228

ACTIVE INGREDIENTS: ISOPROPYL ALCOHOL 7 mL/10 mL
INACTIVE INGREDIENTS: WATER

Alcohol Prep Pad

PURPOSE

For professional and hosptial use

Apply topically as needed to clense intended area.

KEEP OUT OF REACH OF CHILDREN

For professional and hospital use.

INDICATIONS AND USAGE

Apply topically as needed to clense affected area

WARNINGS

For external use only

Discard after single use.

DOSAGE AND ADMINISTRATION

<Apply topically as needed to clense intended area.>

INACTIVE INGREDIENT

Water

ACTIVE INGREDIENT

70% Isopropyl Alcohol

PACKAGE LABEL

Alcohol Prep Pad For professional and hospital use